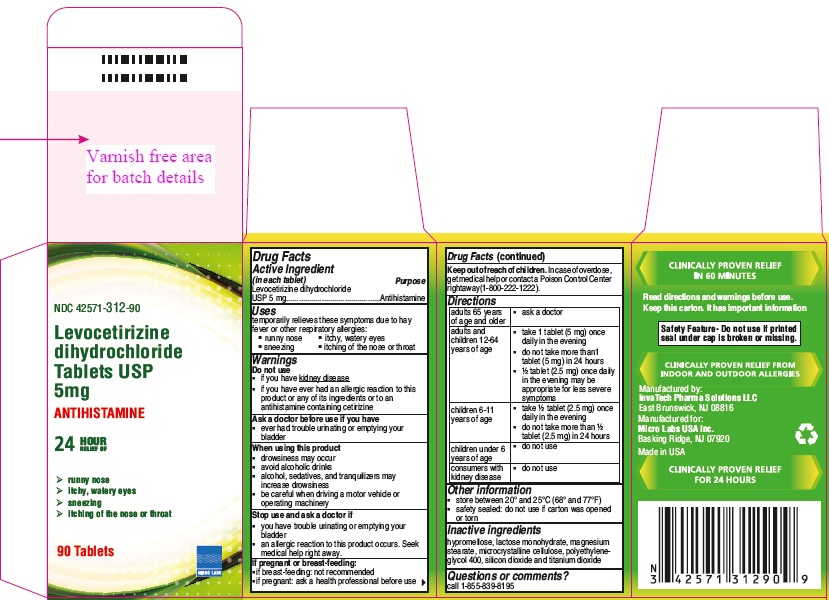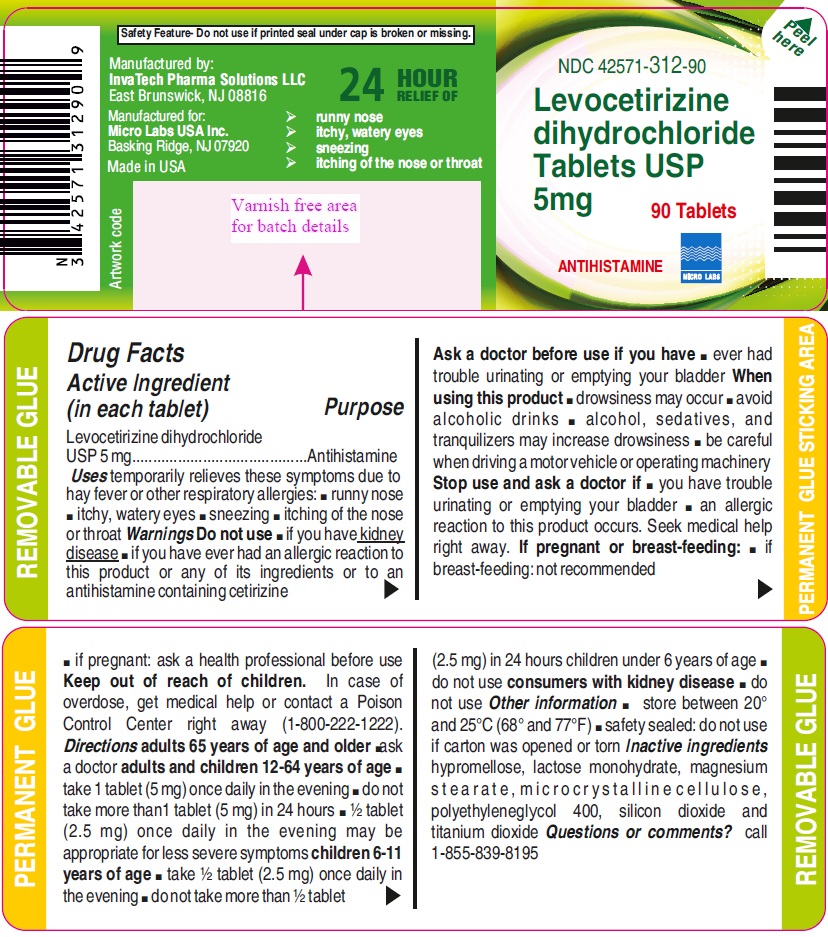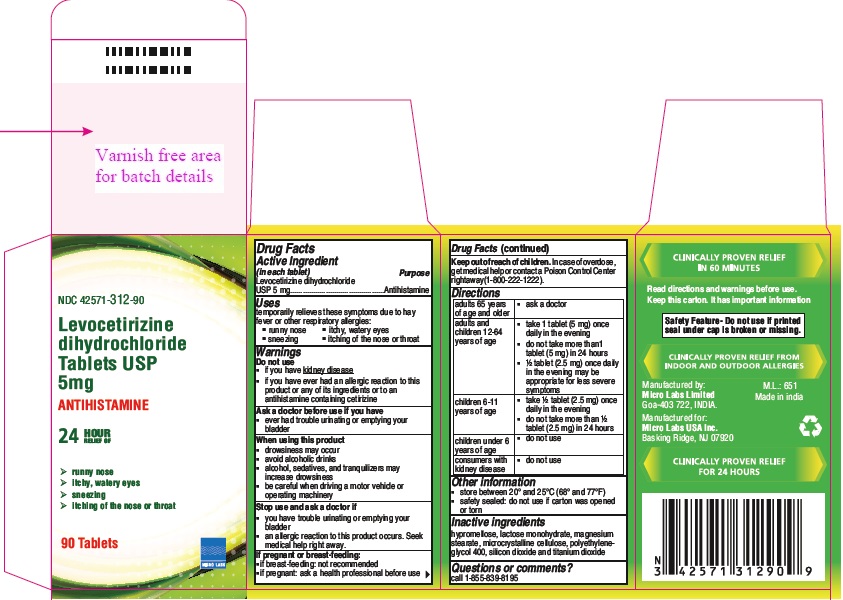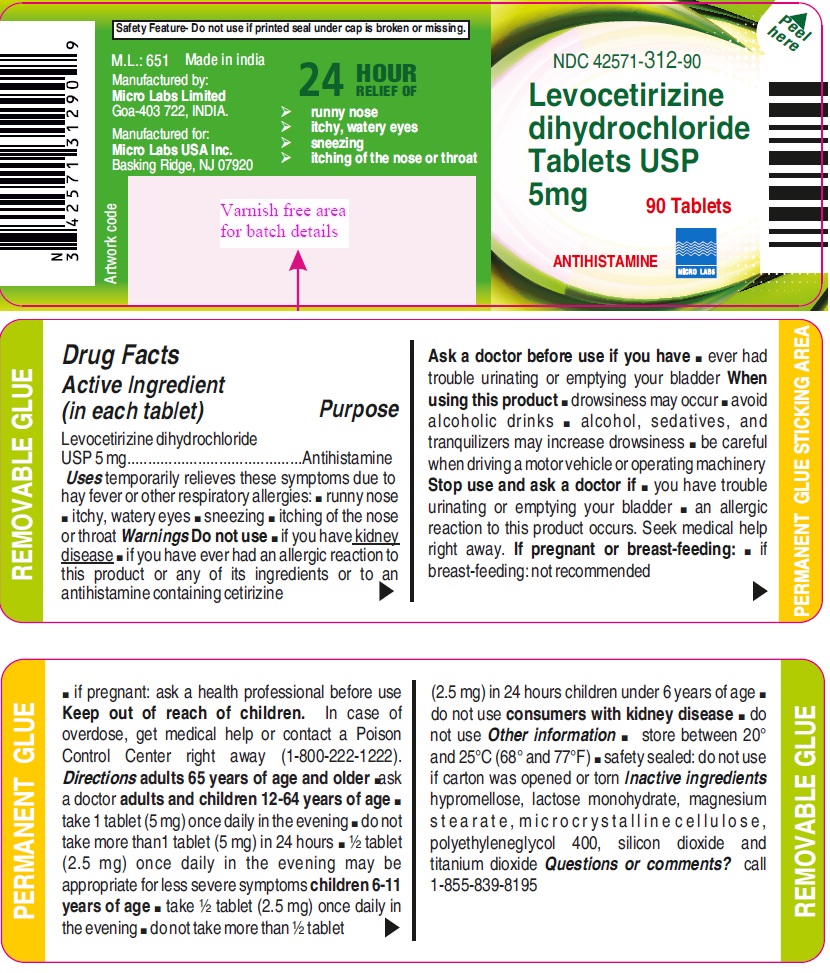 DRUG LABEL: Levocetirizine Dihydrochloride

NDC: 42571-312 | Form: TABLET
Manufacturer: Micro Labs Limited
Category: otc | Type: HUMAN OTC DRUG LABEL
Date: 20250216

ACTIVE INGREDIENTS: LEVOCETIRIZINE DIHYDROCHLORIDE 5 mg/1 1
INACTIVE INGREDIENTS: SILICON DIOXIDE; CELLULOSE, MICROCRYSTALLINE; MAGNESIUM STEARATE; HYPROMELLOSE 2910 (5 MPA.S); TITANIUM DIOXIDE; POLYETHYLENE GLYCOL 400; LACTOSE MONOHYDRATE

Drug Facts

Active ingredient (in each tablet)

Levocetirizine dihydrochloride USP 5 mg

Purpose

Antihistamine

Uses

temporarily relieves these symptoms due to hay fever or other respiratory allergies:

- runny nose
- sneezing
- itchy, watery eyes
- itching of the nose or throat

WARNINGS

Do not use

- if you have kidney disease
- if you have ever had an allergic reaction to this product or any of its ingredients or to an antihistamine containing cetirizine

Ask a doctor before use if you have

- ever had trouble urinating or emptying your bladder

When using this product

- drowsiness may occur
- avoid alcoholic drinks
- alcohol, sedatives, and tranquilizers may increase drowsiness
- be careful when driving a motor vehicle or operating machinery

Stop use and ask a doctor if

- you have trouble urinating or emptying your bladder
- an allergic reaction to this product occurs. Seek medical help right away.

If pregnant or breast-feeding:

- if breast-feeding: not recommended
- if pregnant: ask a health professional before use

Keep out of reach of children.

In case of overdose, get medical help or contact a Poison Control Center right away (1-800-222-1222).

DO NOT USE

- if you have kidney disease
- if you have ever had an allergic reaction to this product or any of its ingredients or to an antihistamine containing cetirizine

DIRECTIONS

adults 65 years of age and older | - ask a doctor
adults and children 12-64 years of age | - take 1 tablet (5 mg) once daily in the evening - do not take more than1 tablet (5 mg) in 24 hours - ½ tablet (2.5 mg) once daily in the evening may be appropriate for less severe symptoms
children 6-11 years of age | - take ½ tablet (2.5 mg) once daily in the evening - do not take more than ½ tablet (2.5 mg) in 24 hours
children under 6 years of age | - do not use
consumers with kidney disease | - do not use

STORAGE

- store between 20° and 25°C (68° and 77°F)
- safety sealed: do not use if carton was opened or torn

Inactive ingredients

hypromellose, lactose monohydrate, magnesium stearate, microcrystalline cellulose, polyethylene glycol 400, silicon dioxide, and titanium dioxide

Questions or comments?

call 1-855-839-8195

PRINCIPAL DISPLAY PANEL

MICRO LABS LIMITED
Container
NDC- 42571-312-90
Levocetirizine dihydrochloride Tablets USP
5mg
Antihistamine

90 Tablets MICRO LABS
Container-Carton

NDC- 42571-312-90
Levocetirizine dihydrochloride Tablets USP
5mg
Antihistamine

90 Tablets MICRO LABS
INVATECH PHARMA SOLUTIONS LLC
Container

NDC- 42571-312-90
Levocetirizine dihydrochloride Tablets USP
5mg
Antihistamine

90 Tablets MICRO LABS
Container-Carton

NDC- 42571-312-90
Levocetirizine dihydrochloride Tablets USP
5mg
Antihistamine

90 Tablets MICRO LABS